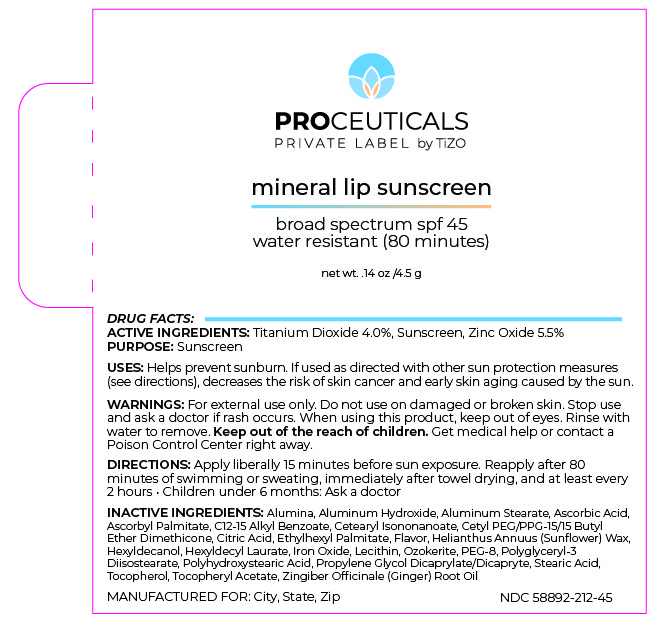 DRUG LABEL: PROCEUTICALS PRIVATE LABEL by TiZO mineral lip sunscreen
NDC: 58892-212 | Form: STICK
Manufacturer: Fallien Cosmeceuticals, LTD
Category: otc | Type: HUMAN OTC DRUG LABEL
Date: 20240716

ACTIVE INGREDIENTS: ZINC OXIDE 55 mg/1 g; TITANIUM DIOXIDE 40 mg/1 g
INACTIVE INGREDIENTS: ALUMINUM OXIDE; .ALPHA.-TOCOPHEROL ACETATE; ALUMINUM HYDROXIDE; ALUMINUM STEARATE; ASCORBIC ACID; ALKYL (C12-15) BENZOATE; CITRIC ACID MONOHYDRATE; HELIANTHUS ANNUUS SEED WAX; HEXYL LAURATE; FERRIC OXIDE RED; LECITHIN, SUNFLOWER; POLYETHYLENE GLYCOL 400; POLYGLYCERYL-3 DIISOSTEARATE; POLYHYDROXYSTEARIC ACID (2300 MW); ASCORBYL PALMITATE; CETEARYL ISONONANOATE; CETYL PEG/PPG-10/1 DIMETHICONE (HLB 4); DIPROPYLENE GLYCOL CAPRYLATE; KIWI FRUIT OIL; HEXYLDECANOL; ETHYLHEXYL PALMITATE; CITRUS AURANTIIFOLIA FRUIT OIL; CERESIN; STEARIC ACID; TOCOPHEROL; GINGER OIL

ACTIVE INGREDIENTS:
Titanium Dioxide 4%
Zinc Oxide 5.5%

PURPOSE:Sunscreen

DIRECTIONS:
• Apply liberally 15 minutes before sun exposure.
• Reapply:
• After 80 minutes of swimming or sweating
• Immediately after towel drying
• At least every 2 hours
• Children under 6 months: Ask a doctor

INACTIVE INGREDIENTS:

Alumina, Aluminum Hydroxide, Aluminum Stearate, Asorbic Acid, Ascorbyl Palmitate, C Alkyl Benzoate, Cetearyl Isononanoate, Cetyl PEG/PPG-15/15 Butyl Ether Dimethicone, Citric Acid, Dipropylene Glycol Dicaprylate-Caprate. Ethylhexyl Palmitate, Flavor, Helianthus Annuus (Sunflower) Seed Wax, Hexyldecanol, Hexyldecyl Laurate, Iron Oxide, Lecithin, Ozokerite, PEG-8, Polyglyceryl-3 Disostearate, Polyhydroxystearic Acid, Stearic Acid, Tocopherol, Tocopheryl Acetate, Zingiber Officinale (Ginger) Root Oi

WARNINGS

WARNINGS:For external use only. Do not use on damaged or broken skin. Stop
use and ask a doctor if rash occurs. When using this product, keep out of eyes.
Rinse with water to remove. Keep out of the reach of children. Get medical help
or contact a Poison Control Center right away.

Keep out of the reach of
children.

DOSAGE AND ADMINISTRATION

Helps prevent sunburn. If used as directed with other sun
protection measures (see Directions), decreases the risk of skin
cancer and early skin aging caused by the sun.

Apply liberally 15 minutes before sun exposure.

Principal Display Panel – 53 g Bottle Label

Proceuticals

PRIVATE LABEL by TiZO

non-tinted
mineral sunscreen

broad spectrum spf 40
water resistant (80 minutes)

net wt. 1.8 oz / 53 g

Graphic-Untitled